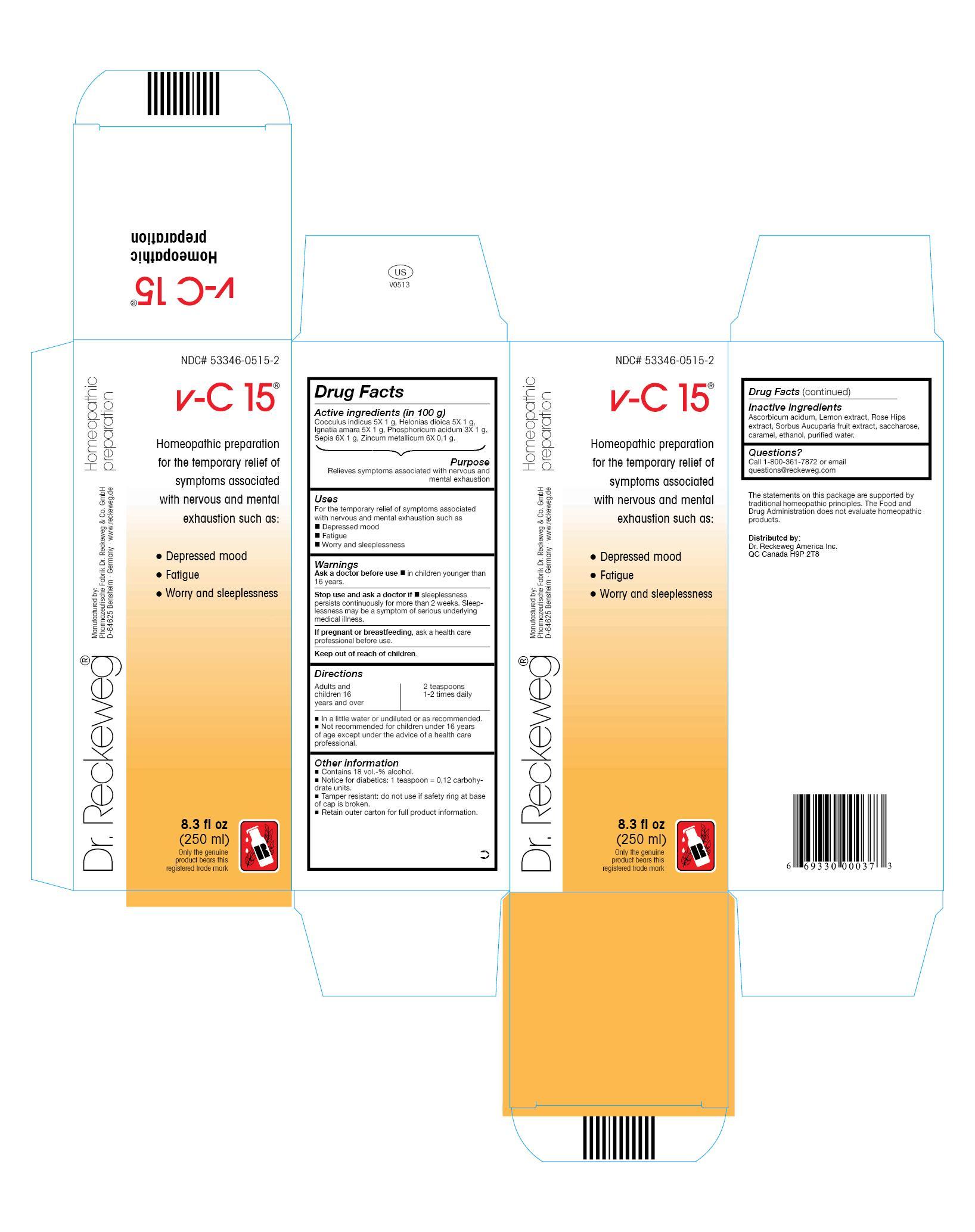 DRUG LABEL: DR. RECKEWEG v-C15
NDC: 53346-0515 | Form: LIQUID
Manufacturer: PHARMAZEUTISCHE FABRIK DR. RECKEWEG & CO
Category: homeopathic | Type: HUMAN OTC DRUG LABEL
Date: 20130524

ACTIVE INGREDIENTS: ANAMIRTA COCCULUS SEED 5 [hp_X]/250 mL; CHAMAELIRIUM LUTEUM ROOT 5 [hp_X]/250 mL; STRYCHNOS IGNATII SEED 5 [hp_X]/250 mL; PHOSPHORIC ACID 3 [hp_X]/250 mL; SEPIA OFFICINALIS JUICE 6 [hp_X]/250 mL; ZINC 6 [hp_X]/250 mL
INACTIVE INGREDIENTS: ASCORBIC ACID; LEMON; ROSA CANINA FRUIT; SORBUS AUCUPARIA FRUIT; SUCROSE; CARAMEL; ALCOHOL; WATER

DR. RECKEWEG v-C 15

Active ingredients
Cocculus indicus 5X 1 g, Helonias dioica 5X 1 g, Ignatia amara 5X 1 g, Phosphoricum acidum 3X 1 g, Sepia 6X 1 g, Zincum metallicum 6X 0,1 g, in 100 g.

Purpose

Relieves symptoms associated with nervous and mental exhaustion

Uses

For the temporary relief of symptoms associated with nervous and mental exhaustion such as:

- Depressed mood
- Fatigue
- Worry and sleeplessness

Warnings

Ask a doctor before use

- in children younger than 16 years.

Stop use and ask a doctor if

- sleeplessness persists continuously for more than 2 weeks. Sleeplessness may be a symptom of serious underlying medical illness.

PREGNANCY OR BREAST FEEDING

If pregnant or breastfeeding, ask a health care professional before use.

Keep out of reach of children.

Directions
Adults and children ≥ 16 years: 2 teaspoons 1-2 times daily in a little water or undiluted or as recommended.

Not recommended for children under 16 years of age except under the advice of a health care professional.

Other information

- Contains 18 vol.-% alcohol.
- Notice for diabetics: 1 teaspoon = 0,12 carbohydrate units.
- Tamper resistant: do not use if safety ring at base of cap is broken.
- Retain outer carton for full product information.

Inactive ingredients

Ascorbicum acidum, Lemon extract, Rose Hips extract, Sorbus Aucuparia fruit extract, saccharose, caramel, ethanol, purified water.

Questions?

Call 1-800-361-7872 or email questions@reckeweg.com

PACKAGE LABEL

NDC# 53346-0515-2

Dr. Reckeweg v-C 15

Homeopathic preparation for the temporary relief of symptoms associated with nervous and mental exhaustion such as:

- Depressed mood
- Fatigue
- Worry and sleeplessness

Manufactured by:

Pharmazeutische Fabrik Dr. Reckeweg Co. GmbH

D-64625 Bensheim

Germany

www.reckeweg.de

8.3 fl oz

(250 ml)